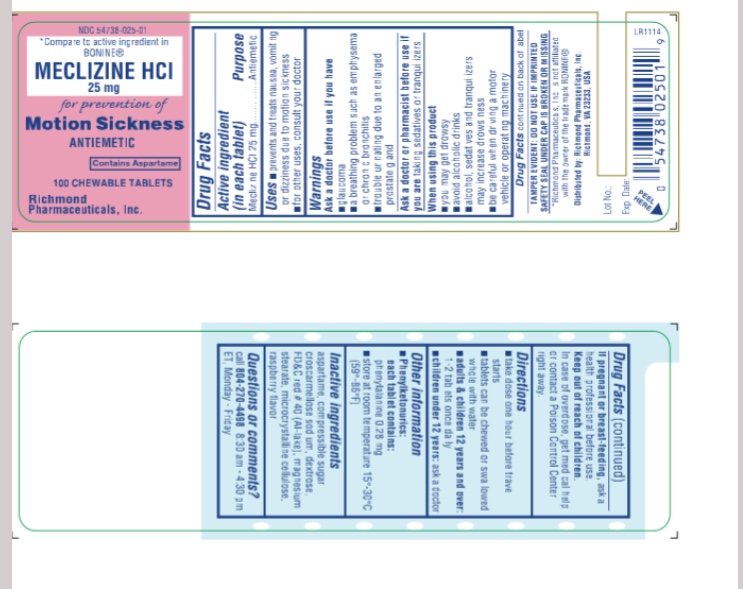 DRUG LABEL: Meclizine HCL
NDC: 54738-025 | Form: TABLET, CHEWABLE
Manufacturer: Richmond Pharmaceuticals, Inc.
Category: otc | Type: HUMAN OTC DRUG LABEL
Date: 20171030

ACTIVE INGREDIENTS: MECLIZINE HYDROCHLORIDE 25 mg/1 1
INACTIVE INGREDIENTS: ASPARTAME; CROSCARMELLOSE SODIUM; DEXTROSE; FD&C RED NO. 40; RASPBERRY; MAGNESIUM STEARATE; MICROCRYSTALLINE CELLULOSE; SUCROSE

Motion Sickness

Active ingredient

Meclizine Hydrochloride 25 mg

Purpose

Antiemetic

Uses

For the prevention and treatment of nausea, vomiting or dizziness associated with motion sickness. For other uses consult your doctor

Warnings

Ask a doctor before use if you have

- glaucoma
- a breathing problem such as emphysema or chronic bronchitis
- trouble urinating due to an elarged prostate gland

Ask a doctor or pharmacist before use if you are taking sedatives or tranquilizers

When using this product

- you may get drowsy
- avoid alcoholic drinks
- alcohol, sedatives and tranquilizers may increse drowsiness
- be careful when driving a moor vehicle or operating machinery

Directions

take dose one hour before travel starts
tablets can be chewed or swallowed whole with water

adults & children 12 years and over:

- take 1-2 tablets once daily

children under 12 years:

- ask a doctor

Keep out of reach of children.

In case of overdose, get medical help or contact a Poison Control Center right away.

OTHER INFORMATION

Phenylketonurics:
each tablet contains:
phenylalanine 0.28 mg
store at room temparature 15 - 30 °C

Questions or Comments

Call 804-270-4498, 8.30 am-4.30 pm ET, Monday - Friday
TAMPER EVIDENT: DO NOT USE IF IMPRINTED SAFETY SEAL UNDER CAP IS BROKEN OR MISSING

Inactive ingredients

Aspartame, compressible sugar, croscarmellose sodium, dextrose, FD&C red 40 (al-lake), magnesium stearate, microcrystalline cellulose, raspberry flavor

Package/Label Principal Display Panel

NDC : 54738-025-01- 100 CHEW TABS

NDC : 54738-025-03- 1000 CHEW TABS